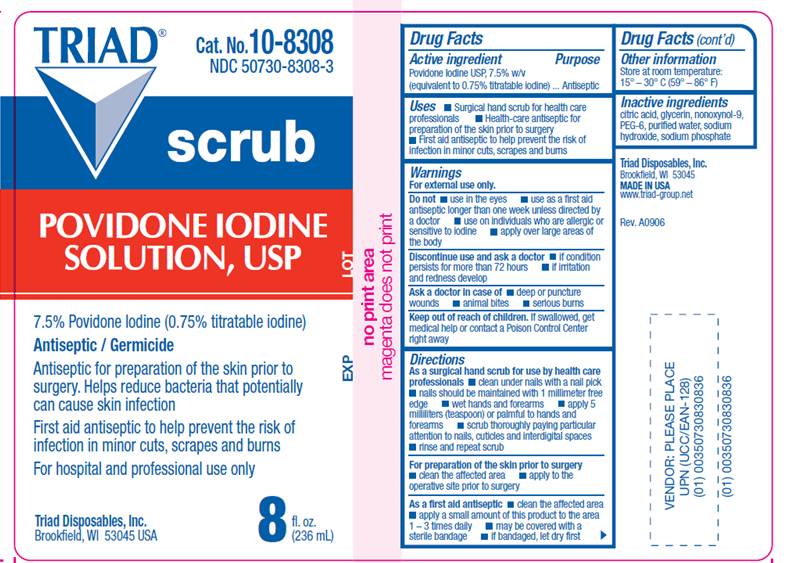 DRUG LABEL: Triadine
NDC: 50730-8308 | Form: SOLUTION
Manufacturer: H and P Industries, Inc. dba Triad Group
Category: otc | Type: HUMAN OTC DRUG LABEL
Date: 20091124

ACTIVE INGREDIENTS: povidone-iodine .075 mL/1 mL
INACTIVE INGREDIENTS: citric acid monohydrate; glycerin; nonoxynol-9; polyethylene glycol 300; sodium hydroxide; sodium phosphate, monobasic, monohydrate; water

DRUG FACTS

ACTIVE INGREDIENT

Povidone Iodine USP 7.5% w/v (equivalent to 0.75% titratable iodine)

PURPOSE

Antiseptic

USES

- Surgical hand scrub for health care processionals
- Health Care Antiseptic for preparation of the skin prior to surgery
- First Aid Antiseptic to help prevent the risk of infection in minor cuts, scrapes and burns

WARNINGS

For external use only.

Do not

- use in the eyes
- apply over large areas of the body
- use on individuals who are allergic or sensitive to iodine
- use as a first aid antiseptic for longer than 1 week unless directed by a doctor

Ask a doctor in case of

- deep or puncture wounds
- animal bites
- serious burns

Stop use and ask a doctor

- if condition persists for more than 72 hours
- if irritation and redness develop

Keep out of reach of children

If swallowed, get medical help or contact a Poison Control Center right away.

DIRECTIONS

As a surgical hand scrub for use by health care professionals

- clean under nails with a nail pick
- nails should be maintained with 1 millimeter free edge
- wet hands and forearms
- apply milliliter (teaspoon) or palmful to hands and forearms
- scrub thoroughly paying particular attention to nails, cuticles and interdigital spaces
- rinse and repeat scrub

For preparation of the skin prior to surgery

- clean the affected area
- apply to the operative site prior to surgery

As a first aid antiseptic

- clean the affected area
- apply a small amount of this product to the area 1-3 times daily
- may be covered with a sterile bandage
- if bandaged, let dry first

OTHER INFORMATION

Store at room temperature 15° - 30° C (59° - 86° F)

INACTIVE INGREDIENTS

citric acid, glycerin, nonoxynol-9, PEG-300, sodium hydroxide, sodium phosphate, water

LABEL INFORMATION

Triad
Cat. No. 10-8308
NDC 50730-8308-3
scrub
POVIDONE IODINE
SOLUTION, USP
7.5% Povidone Iodine (0.75% titratable iodine)
Antiseptic / Germicide
Antiseptic for preparation of the skin prior to surgery. Helps reduce bacteria that potentially can cause skin infection
First aid antiseptic to help prevent the risk of infection in minor cuts, scrapes and burns
For hospital and professional use only
Triad Disposables, Inc.
Brookfield, WI 53045 USA
8 fl. oz.(236 ml)